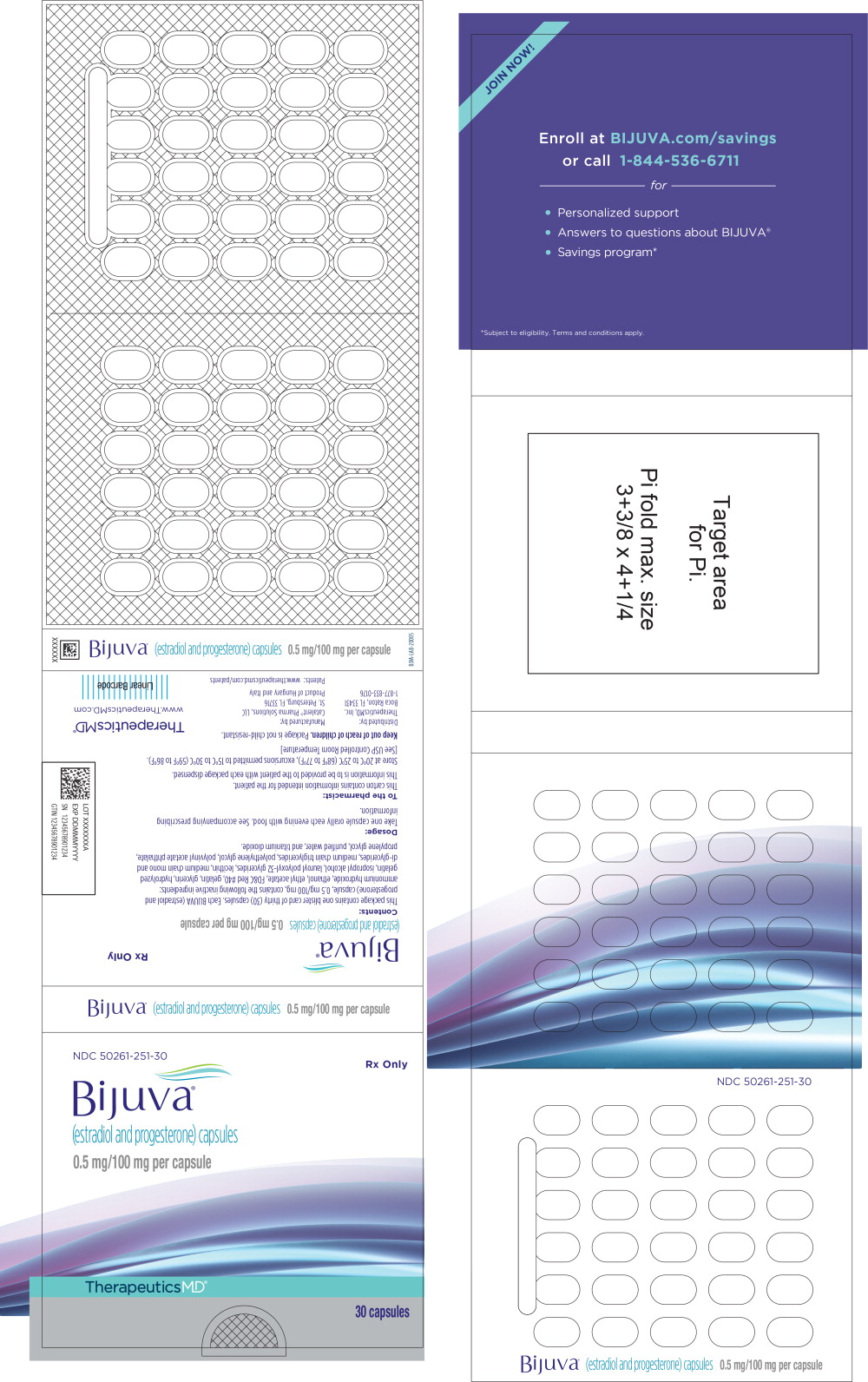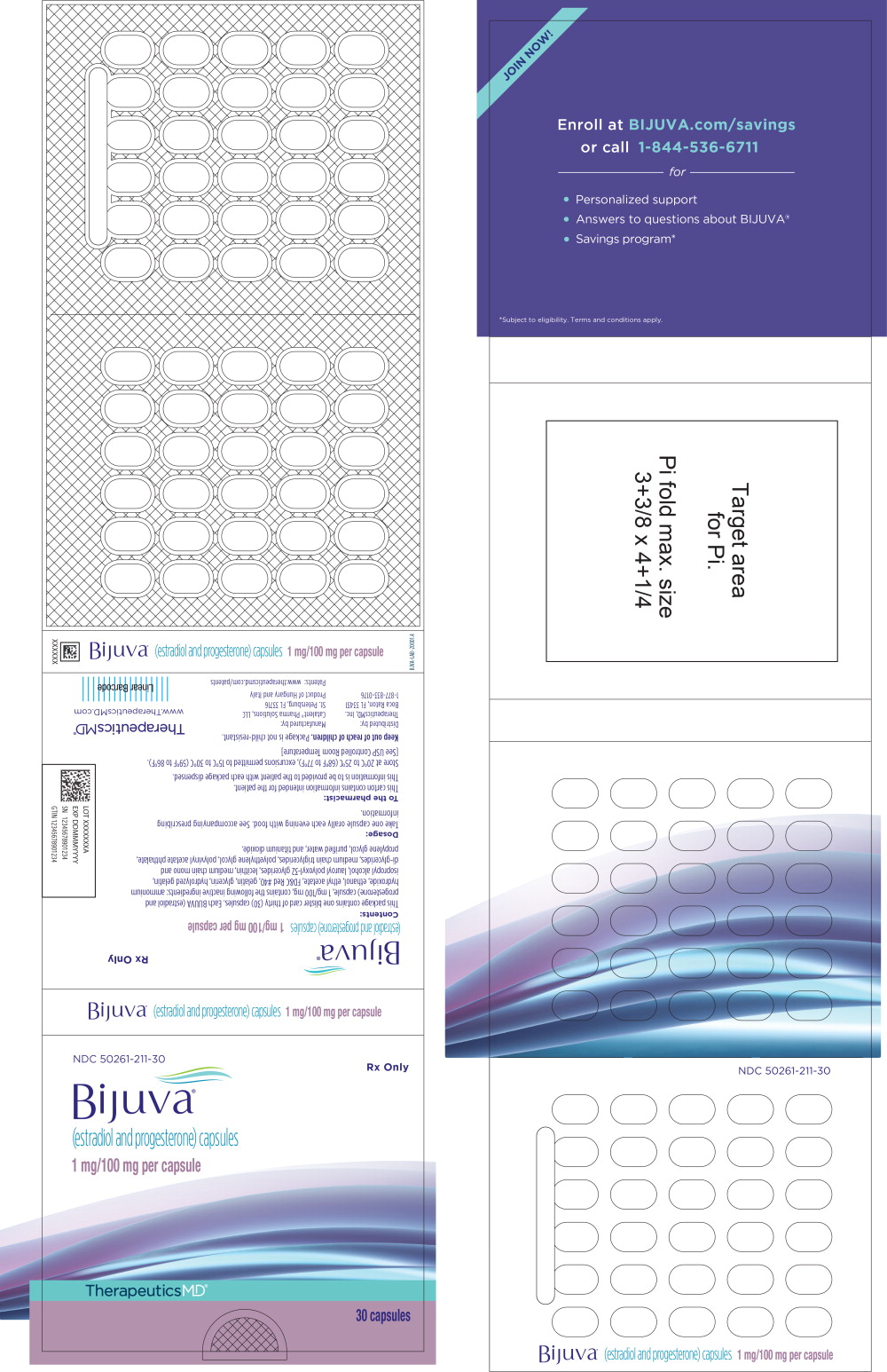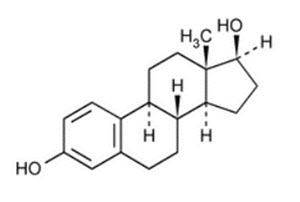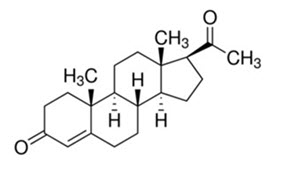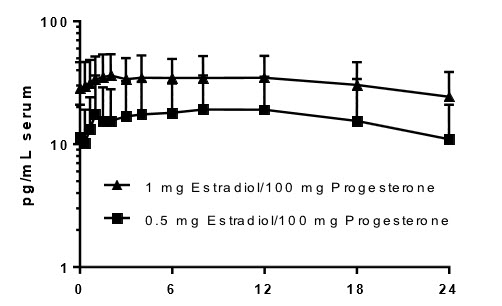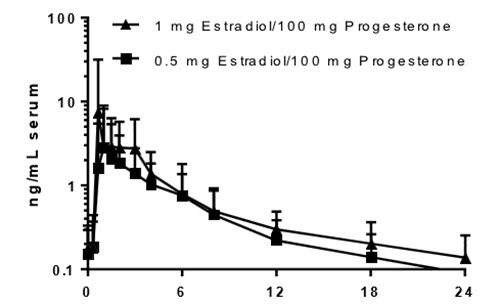 DRUG LABEL: Bijuva
NDC: 50261-211 | Form: CAPSULE
Manufacturer: Mayne Pharma LLC
Category: prescription | Type: HUMAN PRESCRIPTION DRUG LABEL
Date: 20260225

ACTIVE INGREDIENTS: ESTRADIOL 1 mg/1 1; PROGESTERONE 100 mg/1 1
INACTIVE INGREDIENTS: GLYCERYL MONO- AND DICAPRYLOCAPRATE; LAUROYL PEG-32 GLYCERIDES; GELATIN TYPE B BOVINE (200 BLOOM); GLYCERIN; GELATIN, UNSPECIFIED; WATER; TITANIUM DIOXIDE; FD&C RED NO. 40; ALCOHOL; ETHYL ACETATE; PROPYLENE GLYCOL; POLYVINYL ACETATE PHTHALATE; ISOPROPYL ALCOHOL; POLYETHYLENE GLYCOL, UNSPECIFIED; AMMONIA; MEDIUM-CHAIN TRIGLYCERIDES; SOYBEAN LECITHIN

HIGHLIGHTS OF PRESCRIBING INFORMATION

These highlights do not include all the information needed to use BIJUVA safely and effectively. See full prescribing information for BIJUVA.
BIJUVA® (estradiol and progesterone) capsules, for oral use
Initial U.S. Approval: 2018

RECENT MAJOR CHANGES

Boxed Warning, Cardiovascular Disorders, Probable
Dementia, Breast Cancer, and Endometrial Cancer | removed 2/2026
Dosage and Administration (2) | 2/2026
Contraindications (4) | 2/2026
Warnings and Precautions, Cardiovascular Disorders (5.1) | 2/2026
Warnings and Precautions, Malignant Neoplasms (5.2) | 2/2026
Warnings and Precautions, Probable Dementia | removed 2/2026
Warnings and Precautions, Addition of a Progestogen
When a Woman Has Not Had a Hysterectomy | removed 2/2026

1 INDICATIONS AND USAGE

BIJUVA is a combination of an estrogen and progesterone indicated in a woman with a uterus for the treatment of moderate to severe vasomotor symptoms due to menopause. (1.1)

2 DOSAGE AND ADMINISTRATION

One capsule orally each evening with food. (2.1)

3 DOSAGE FORMS AND STRENGTHS

Capsules: 0.5 mg estradiol/100 mg progesterone or 1 mg estradiol/100 mg progesterone. (3)

4 CONTRAINDICATIONS

- Undiagnosed abnormal genital bleeding (4, 5.2)
- Breast cancer or a history of breast cancer (4, 5.2)
- Estrogen-dependent neoplasia (4, 5.2)
- Active DVT, PE, or history of these conditions (4, 5.1)
- Active arterial thromboembolic disease (for example, stroke and MI), or a history of these conditions (4, 5.1)
- Known anaphylactic reaction, angioedema, or hypersensitivity to BIJUVA (4, 5.15)
- Hepatic impairment or disease (4, 5.8)
- Protein C, protein S, or antithrombin deficiency, or other known thrombophilic disorders (4)

5 WARNINGS AND PRECAUTIONS

- Cardiovascular Disorders: Increased risks of PE, DVT, stroke, and MI are reported with estrogen plus progestin therapy. Manage risk factors for arterial vascular disease and/or venous thromboembolisum. Discontinue if an arterial or venous thrombotic or thromboembolic event occurs. (5.1)
- Malignant Neoplasms: Assess risk and provide surveillance measures for breast cancer, such as breast examinations and mammography. (5.2)
- Estrogens increase the risk of gallbladder disease. (5.3)
- Discontinue estrogen if severe hypercalcemia, loss of vision, severe hypertriglyceridemia, or cholestatic jaundice occurs. (5.4, 5.5, 5.7, 5.8)
- Monitor thyroid function in women on thyroid replacement hormone therapy. (5.9, 5.15)

6 ADVERSE REACTIONS

The most common adverse reactions with BIJUVA (incidence ≥ 3% of women and greater than placebo) are: breast tenderness, headache, nausea, vaginal bleeding, vaginal discharge and pelvic pain. (6.1)

To report SUSPECTED ADVERSE REACTIONS, contact Mayne Pharmaat 1-844-825-8500 or FDA at 1-800-FDA-1088 or www.fda.gov/medwatch.

7 DRUG INTERACTIONS

Inducers and inhibitors of CYP3A4 may affect estrogen drug metabolism and decrease or increase the estrogen plasma concentration. (7)

FULL PRESCRIBING INFORMATION

2 DOSAGE AND ADMINISTRATION

The timing of BIJUVA initiation can affect the overall risk-benefit profile. Consider initiating BIJUVA in women < 60 years old or < 10 years from onset of menopause [see Warnings and Precautions (5), Adverse Reactions (6.1), Use in Specific Populations (8.5) and Clinical Studies (14)].

Take a single BIJUVA capsule orally each evening with food. Generally, start therapy with BIJUVA 0.5 mg estradiol/100 mg progesterone dosage strength. Make dosage adjustment based on the clinical response. Attempt to taper or discontinue BIJUVA at 3 to 6 month intervals.

3 DOSAGE FORMS AND STRENGTHS

BIJUVA capsules, 0.5 mg/100 mg, are oval shaped, opaque, light pink on one side, dark pink on the other side, and printed with "5C1" in white ink.

BIJUVA capsules, 1 mg/100 mg, are oval shaped, opaque, light pink on one side, dark pink on the other side, and printed with "1C1" in white ink.

4 CONTRAINDICATIONS

BIJUVA is contraindicated in women with any of the following conditions:

- Abnormal genital bleeding of unknown etiology [see Warnings and Precautions (5.2)].
- Breast cancer or a history of breast cancer [see Warnings and Precautions (5.2)].
- Estrogen-dependent neoplasia [see Warnings and Precautions (5.2)].
- Active deep vein thrombosis (DVT), pulmonary embolisum (PE), or history of these conditions [see Warnings and Precautions (5.1)].
- Active arterial thromboembolic disease (for example, stroke, myocardial infarction (MI)), or a history of these conditions [see Warnings and Precautions (5.1)].
- Known anaphylactic reaction, angioedema, or hypersensitivity to BIJUVA.
- Hepatic impairment or disease [see Warnings and Precautions (5.8)]
- Known thrombophilic disorders, such as protein C, protein S, or antithrombin deficiency

5 WARNINGS AND PRECAUTIONS

5.1 Cardiovascular Disorders

BIJUVA is contraindicated in females with active DVT, PE, arterial thromboembolic disease (e.g., stroke, MI) disease, or a history of these conditions [see Contraindications (4)]. Immediately discontinue BIJUVA if a PE, DVT, stroke, or MI occurs or is suspected.

If feasible, discontinue BIJUVA at least 4 to 6 weeks before surgery of the type associated with an increased risk of thromboembolism, or during periods of prolonged immobilization.

The safety and efficacy of BIJUVA for the prevention of cardiovascular disorders has not been established [see Clinical Studies (14.4)].

The Women's Health Initiative (WHI) estrogen plus progestin trial reported increased risks of PE, DVT, stroke, and MI in postmenopausal women (50 to 79 years of age, average age 63.4 years) during the 5.6 years of treatment with daily oral conjugated estrogens (CE) [0.625 mg] combined with medroxyprogesterone acetate (MPA) [2.5 mg], relative to placebo. Analyses were also conducted in women aged 50-59 years, a group of women more likely to present with new onset of moderate to severe VMS compared to women in other age groups in the trial [see Clinical Studies (14.4)].

Only daily oral 0.625 mg CE and 2.5 mg MPA were studied in the estrogen plus progestin trial of the WHI. Therefore, the relevance of the WHI findings regarding adverse cardiovascular events to lower CE plus other MPA doses, other routes of administration, or other estrogen plus progestogen products is not known. Without such data, it is not possible to definitively exclude these risks or determine the extent of these risks for other products.

Venous Thromboembolism

In women aged 50-59 years, the WHI estrogen plus progestin trial reported a relative risk for PE of 2.05 (95% confidence interval [CI], 0.89-4.71) for CE/MPA compared to placebo, with a risk difference of 6 per 10,000 women-years (WYs; 11 versus 5). The relative risk for DVT was 3.01 (95% CI, 1.36-6.66) in those receiving CE/MPA compared to placebo, with a risk difference of 10 per 10,000 WYs (15 versus 5) [see Clinical Studies (14.4)].

In the overall study population of women aged 50-79 years (average 63.4 years), the trial reported a relative risk for PE of 1.98 (95% CI, 1.36-2.87) for CE/MPA compared to placebo, with a risk difference of 9 per 10,000 WYs (18 versus 9). The relative risk for DVT was 1.87 (95% CI, 1.37-2.54) for CE/MPA compared to placebo, with a risk difference of 12 per 10,000 WYs (25 versus 14) [see Clinical Studies (14.4)].

Stroke

In women aged 50-59 years, the WHI estrogen plus progestin trial reported a relative risk for stroke of 1.51 (95% CI, 0.81-2.82) for CE/MPA compared to placebo, with a risk difference of 5 per 10,000 WYs (15 versus 10) [see Clinical Studies (14.4)].

In the overall study population of women aged 50-79 years (average 63.4 years), the WHI estrogen plus progestin trial reported relative risk for stroke of 1.37 (95% CI, 1.07-1.76) for CE/MPA compared to placebo, with a risk difference of 9 per 10,000 WYs (33 versus 24) [see Clinical Studies (14.4)].

Coronary Heart Disease

In women 50 to 59 years of age, the WHI estrogen plus progestin trial reported a relative risk for coronary heart disease (CHD) events (defined as nonfatal MI, silent MI, or CHD death) of 1.34 (95% CI, 0.82-2.19) for CE/MPA compared placebo, with a risk difference of 5 per 10,000 WYs (23 versus 17).

In the overall study population of women aged 50-79 years (average 63.4 years), the trial reported a relative risk of CHD of 1.18 (95% CI, 0.95-1.45) for CE/MPA compared to placebo, with a risk difference of 6 per 10,000 WYs (41 versus 35) [see Clinical Studies (14.4)].

In the Heart and Estrogen/Progestin Replacement Study (HERS) and open label extension (HERS II), postmenopausal women with documented heart disease (n=2,763, average age 66.7 years) received daily CE (0.625 mg) plus MPA or placebo. In Year 1, there were more CHD events in the CE plus MPA-treated group than placebo; however, rates of CHD events were comparable among both groups for the remainder of the duration of the studies (average total follow-up of 6.8 years).^(2, 3)

5.2 Malignant Neoplasms

Breast Cancer

BIJUVA is contraindicated in women with breast cancer, a history of breast cancer, or estrogen-dependent neoplasia [see Contraindications (4)].

Discontinue BIJUVA if a hormone-sensitive malignancy is diagnosed.The use of estrogen plus progestin therapy has been reported to result in an increase in abnormal mammograms requiring further evaluation.

Only daily oral CE 0.625 mg and MPA 2.5 mg were studied in the estrogen plus progestin trial of the WHI. Therefore, the relevance of the WHI findings regarding breast cancer to lower CE plus other MPA doses, other routes of administration, or other estrogen plus progestogen products is not known. Without such data, it is not possible to definitively exclude these risks or determine the extent of these risks for other products.

In women 50-59 years of age, the WHI estrogen plus progestin trial reported a relative risk for invasive breast cancer of 1.21 (95% CI, 0.81-1.80) for CE/MPA compared to placebo, with a risk difference of 6 per 10,000 WYs (33 versus 27). In this age group, among those who reported no prior use of hormone therapy, the relative risk was 1.06 (95% CI, 0.67-1.67) for CE/MPA compared to placebo, with a risk difference of 2 per 10,000 WYs (33 versus 31) [see Clinical Studies (14.4)].

In the overall study population of women aged 50-79 years (average 63.4 years), the WHI estrogen plus progestin trial reported a relative risk for invasive breast cancer of 1.24 (95% CI, 1.01-1.53) for CE/MPA compared to placebo, with a risk difference of 9 per 10,000 WYs (43 versus 35). In the overall study population, among women who reported prior use of hormone therapy, the relative risk of invasive breast cancer was 1.85 (95% CI, 1.18-2.90) for CE/MPA compared to placebo, with a risk difference of 21 per 10,000 WYs (46 versus 25). Among women who reported no prior use of hormone therapy, the relative risk of invasive breast cancer was 1.09 (95% CI, 0.86-1.39), with a risk difference of 4 per 10,000 WYs (40 versus 36). Invasive breast cancers were larger, were more likely to be node positive, and were diagnosed at a more advanced stage in the CE/MPA group compared with the placebo group. Metastatic disease was rare, with no apparent difference between the two groups. Other prognostic factors, such as histologic subtype, grade and hormone receptor status did not differ between the groups. Extension of the WHI trial also demonstrated increased breast cancer risk associated with estrogen plus progestin therapy [see Clinical Studies (14.4)].^1

Consistent with the WHI trial, observational studies have also reported an increased risk of breast cancer with estrogen plus progestin therapy. A large meta-analysis including 24 prospective studies of postmenopausal women comparing current use of estrogen plus progestin products with use duration of 5 to 14 years (average of 9 years) versus never use reported a relative risk for breast cancer of 2.08 (95% CI, 2.02-2.15). These studies have not generally found the risk of breast cancer to be different among the various estrogen plus progestin combinations, doses, or routes of administration.^4

Regarding breast cancer mortality, the WHI estrogen plus progestin trial did not show a statistically significant difference between CE/MPA and placebo. The trial reported a relative risk of 1.35 (95% CI, 0.94-1.95) for CE/MPA compared to placebo, with a risk difference of 1 per 10,000 WYs (5 versus 4) after a median of 19 years of cumulative follow-up [see Clinical Studies (14.4)].

Ovarian Cancer

Comparing CE/MPA to placebo, women 50-59 years of age had a relative risk for ovarian cancer of 0.30 (95% CI, 0.06-1.47) and the risk difference was -3 per 10,000 WYs (1 versus 4) [see Clinical Studies (14.4)].

In the overall WHI study population of women aged 50-79 years (average 63.4 years), the WHI estrogen plus progestin trial reported a relative risk for ovarian cancer of 1.41 (95% CI, 0.75-2.66) for CE/MPA versus placebo after an average follow-up of 5.6 years. The risk difference was 1 per 10,000 WYs (5 versus 4) [see Clinical Studies (14.4)].

A large meta-analysis including 17 prospective studies of postmenopausal women compared current use of estrogen plus progestin products versus never use and reported a relative risk for ovarian cancer of 1.37 (95% CI, 1.26-1.48). The duration of hormone therapy use that was associated with an increased risk of ovarian cancer is unknown.^5

5.3 Gallbladder Disease

A 2- to 4-fold increase in the risk of gallbladder disease requiring surgery in postmenopausal women receiving estrogens has been reported.

5.4 Hypercalcemia

Estrogen administration may lead to severe hypercalcemia in women with breast cancer and bone metastases. Discontinue estrogens, including BIJUVA if hypercalcemia occurs, and take appropriate measures to reduce the serum calcium level.

5.5 Visual Abnormalities

Retinal vascular thrombosis has been reported in women receiving estrogens. Discontinue BIJUVA pending examination if there is a sudden partial or complete loss of vision, or a sudden onset of proptosis, diplopia, or migraine. Permanently discontinue estrogens, including BIJUVA, if examination reveals papilledema or retinal vascular lesions.

5.6 Elevated Blood Pressure

In a small number of case reports, substantial increases in blood pressure have been attributed to idiosyncratic reactions to estrogens. In a large, randomized, placebo-controlled clinical trial, a generalized effect of estrogens on blood pressure was not seen.

5.7 Exacerbation of Hypertriglyceridemia

In women with pre-existing hypertriglyceridemia, estrogen therapy may be associated with elevations of plasma triglycerides leading to pancreatitis. Discontinue BIJUVA if pancreatitis occurs.

5.8 Hepatic Impairment and/or Past History of Cholestatic Jaundice

Estrogens may be poorly metabolized in women with hepatic impairment. Exercise caution in any woman with a history of cholestatic jaundice associated with past estrogen use or with pregnancy. In the case of recurrence of cholestatic jaundice, discontinue BIJUVA.

5.9 Exacerbation of Hypothyroidism

Estrogen administration leads to increased thyroid-binding globulin (TBG) levels. Women with normal thyroid function can compensate for the increased TBG by making more thyroid hormone, thus maintaining free T4 and T3 serum concentrations in the normal range. Women dependent on thyroid hormone replacement therapy who are also receiving estrogens may require increased doses of their thyroid replacement therapy. Monitor thyroid function in these women during treatment with BIJUVA to maintain their free thyroid hormone levels in an acceptable range.

5.10 Fluid Retention

Estrogens plus progestogens may cause some degree of fluid retention. Monitor any woman with a condition(s) that might predispose her to fluid retention, such as cardiac or renal impairment.

Discontinue estrogen plus progestogen therapy, including BIJUVA, with evidence of medically concerning fluid retention.

5.11 Hypocalcemia

Estrogen-induced hypocalcemia may occur in women with hypoparathyroidism. Consider whether the benefits of estrogen therapy, including BIJUVA, outweigh the risks in such women.

5.12 Hereditary Angioedema

Exogenous estrogens may exacerbate symptoms of angioedema in women with hereditary angioedema. Consider whether the benefits of estrogen therapy, including BIJUVA, outweigh the risks in such women.

5.13 Exacerbation of Other Conditions

Estrogen therapy, including BIJUVA, may cause an exacerbation of asthma, diabetes mellitus, epilepsy, migraine, porphyria, systemic lupus erythematosus, and hepatic hemangiomas.

Consider whether the benefits of estrogen therapy outweigh the risks in women with such conditions.

5.14 Laboratory Tests

Serum follicle stimulating hormone (FSH) and estradiol levels have not been shown to be useful in the management of postmenopausal women with moderate to severe vasomotor symptoms.

5.15 Drug Laboratory Test Interactions

- Accelerated prothrombin time, partial thromboplastin time, and platelet aggregation time; increased platelet count; increased factors II, VII antigen, VIII antigen, VIII coagulant activity, IX, X, XII, VII-X complex, II-VII-X complex, and beta-thromboglobulin; decreased levels of antifactor Xa and antithrombin III, decreased antithrombin III activity; increased levels of fibrinogen and fibrinogen activity; increased plasminogen antigen and activity.
- Increased thyroid-binding globulin (TBG) levels leading to increased circulating total thyroid hormone as measured by protein-bound iodine (PBI), T4 levels (by column or by radioimmunoassay) or T3 levels by radioimmunoassay. T3 resin uptake is decreased, reflecting the elevated TBG. Free T4 and free T3 concentrations are unaltered. Women on thyroid replacement therapy may require higher doses of thyroid hormone.
- Other binding proteins may be elevated in serum, for example, corticosteroid binding globulin (CBG), sex hormone-binding globulin (SHBG), leading to increased total circulating corticosteroids and sex steroids, respectively. Free hormone concentrations, such as testosterone and estradiol, may be decreased. Other plasma proteins may be increased (angiotensinogen/renin substrate, alpha-1-antitrypsin, ceruloplasmin).
- Increased plasma high-density lipoprotein (HDL) and HDL2 cholesterol subfraction concentrations, reduced low-density lipoprotein (LDL) cholesterol concentrations, increased triglyceride levels.
- Impaired glucose tolerance.

6 ADVERSE REACTIONS

The following serious adverse reactions are discussed elsewhere in the labeling:

- Cardiovascular Disorders [see Boxed Warning, Warnings and Precautions (5.1)].
- Malignant Neoplasms [see Boxed Warning, Warnings and Precautions (5.2)].

6.1 Clinical Trials Experience

Because clinical trials are conducted under widely varying conditions, adverse reaction rates observed in the clinical trials of a drug cannot be directly compared to rates in the clinical trials of another drug and may not reflect the rates observed in practice.

The safety of estradiol and progesterone capsules was assessed in a 1-year trial that included 1,835 postmenopausal women (1,684 were treated with estradiol and progesterone capsules once daily and 151 women received placebo). Most women (~70%) in the active treatment groups were treated for ≥ 326 days.

Treatment related adverse reactions with an incidence of ≥ 3% in either BIJUVA (estradiol and progesterone) capsules group and numerically greater than those reported in the placebo group are listed in Table 1.

Table 1: Treatment-Emergent Adverse Reactions Reported at a Frequency of ≥ 3% and Numerically More Common in Women Receiving BIJUVA (estradiol and progesterone) 1 mg/100 mg
Preferred Term | BIJUVA 0.5 mg/100 mg (N=424) | BIJUVA 1 mg/100 mg (N=415) | Placebo (N=151)
Breast tenderness | 17 (4.0) | 43 (10.4) | 1 (0.7)
Headache | 17 (4.0) | 14 (3.4) | 1 (0.7)
Nausea | 15 (3.5) | 9 (2.2) | 1 (0.7)
Vaginal bleeding | 10 (2.4) | 14 (3.4) | 0
Vaginal discharge | 8 (1.9) | 14 (3.4) | 1 (0.7)
Pelvic pain | 12 (2.8) | 13 (3.1) | 0

6.2 Postmarketing Experience

The following additional adverse reactions have been identified during post-approval use of BIJUVA. Because these reactions are reported voluntarily from a population of uncertain size, it is not always possible to reliably estimate their frequency or establish a causal relationship to drug exposure.

Gastrointestinal disorders

Abdominal pain and discomfort, abdominal distention, diarrhea, nausea, vomiting.

General disorders and administration site conditions

Fatigue, feeling abnormal, malaise.

Investigations

Weight increased.

Metabolism and nutrition disorders

Fluid retention.

Musculoskeletal and connective tissue disorders

Muscle spasms, pain in extremity.

Nervous system disorders

Dizziness, headache, somnolence.

Psychiatric disorders

Insomnia, sleep disorder.

Reproductive system and breast disorders

Breast pain, breast tenderness, uterine bleeding.

Skin and subcutaneous tissue disorders

Night sweats, pruritus.

Vascular disorders

Hot flush.

7 DRUG INTERACTIONS

In-vitro and in-vivo studies have shown that estrogens and progestins are metabolized partially by cytochrome P450 3A4 (CYP3A4). Therefore, inducers or inhibitors of CYP3A4 may affect estrogen and progestin drug metabolism. Inducers of CYP3A4 such as St. John's wort (Hypericum perforatum) preparations, phenobarbital, carbamazepine, and rifampin may reduce plasma concentrations of estrogens and progestins, possibly resulting in a decrease in therapeutic effects and/or changes in the uterine bleeding profile. Inhibitors of CYP3A4, such as erythromycin, clarithromycin, ketoconazole, itraconazole, ritonavir and grapefruit juice, may increase plasma concentrations of the estrogen or the progestin or both and may result in adverse reactions.

8 USE IN SPECIFIC POPULATIONS

8.1 Pregnancy

Risk Summary

BIJUVA is not indicated for use in pregnancy. There are no data with the use of BIJUVA in pregnant women, however, epidemiologic studies and meta-analyses have not found an increased risk of genital or non-genital birth defects (including cardiac anomalies and limb-reduction defects) following exposure to combined hormonal contraceptives (estrogens and progestins) before conception or during early pregnancy.

In the U.S. general population, the estimated background risk of major birth defects and miscarriage in clinically recognized pregnancies is 2% to 4% and 15% to 20%, respectively.

8.2 Lactation

Risk Summary

Estrogens plus progestogens are present in human milk and can reduce milk production in breast-feeding females. This reduction can occur at any time but is less likely to occur once breast-feeding is well-established. The developmental and health benefits of breastfeeding should be considered along with the mother's clinical need for BIJUVA and any potential adverse effects on the breastfed child from BIJUVA or from the underlying maternal condition.

8.4 Pediatric Use

BIJUVA is not indicated for use in pediatric patients. Clinical studies have not been conducted in the pediatric population.

8.5 Geriatric Use

There have not been sufficient numbers of geriatric women involved in clinical studies utilizing BIJUVA to determine whether those over 65 years of age differ from younger women in their response to BIJUVA.

The Women's Health Initiative Studies

In the WHI estrogen plus progestin trial (daily CE [0.625 mg] plus MPA [2.5 mg] versus placebo), there was a higher relative risk of nonfatal stroke and invasive breast cancer in women greater than 65 years of age [see Clinical Studies (14.4)].

The Women's Health Initiative Memory Study

In the WHIMS ancillary studies of postmenopausal women 65 to 79 years of age, there was an increased risk of developing probable dementia in women receiving estrogen plus progestin [see Clinical Studies (14.5)].

It is unknown whether these findings apply to younger postmenopausal women [see Clinical Studies (14.5)]. The safety and efficacy of BIJUVA for the prevention of dementia has not been established.

10 OVERDOSAGE

Overdosage of estrogen plus progestogen may cause nausea, vomiting, breast tenderness, abdominal pain, drowsiness and fatigue, and withdrawal bleeding may occur in women. Treatment of overdose consists of discontinuation of BIJUVA therapy with institution of appropriate symptomatic care.

11 DESCRIPTION

BIJUVA (estradiol and progesterone) is an oval shaped opaque capsule in which the estradiol is solubilized and the progesterone is micronized and suspended in the mixture of medium chain mono and di-glycerides and lauroyl polyoxyl-32 glycerides.

Each 0.5 mg/100 mg capsule is light pink on one side, dark pink on the other side, and printed with "5C1" in white ink.

Each 1 mg/100 mg capsule is light pink on one side, dark pink on the other side, and printed with "1C1" in white ink.

Estradiol (estra-1,3,5 (10)-triene-3,17β-diol), an estrogen, has a molecular weight of 272.38, and chemical formula C18H24O2.

Progesterone (pregn-4-ene-3, 20-dione) has a molecular weight of 314.47, and chemical formula C21H30O2.

The structural formulas are as follows:

Estradiol

Progesterone

Each BIJUVA (estradiol and progesterone) capsule contains the following inactive ingredients: ammonium hydroxide, ethanol, ethyl acetate, FD&C Red #40, gelatin, glycerin, hydrolyzed gelatin, isopropyl alcohol, lauroyl polyoxyl-32 glycerides, lecithin, medium chain mono and di- glycerides, medium chain triglycerides, polyethylene glycol, polyvinyl acetate phthalate, propylene glycol, purified water, and titanium dioxide.

12 CLINICAL PHARMACOLOGY

12.1 Mechanism of Action

Endogenous estrogens are largely responsible for the development and maintenance of the female reproductive system and secondary sexual characteristics. Although circulating estrogens exist in a dynamic equilibrium of metabolic interconversions, estradiol is the principal intracellular human estrogen and is substantially more potent than its metabolites, estrone and estriol, at the receptor level.

The primary source of estrogen in normally cycling adult women is the ovarian follicle, which secretes 70 to 500 mcg of estradiol daily, depending on the phase of the menstrual cycle. After menopause, most endogenous estrogen is produced by conversion of androstenedione, secreted by the adrenal cortex, to estrone in the peripheral tissues. Thus, estrone and the sulfate conjugated form, estrone sulfate, are the most abundant circulating estrogens in postmenopausal women.

Estrogens act through binding to nuclear receptors in estrogen-responsive tissues. To date, two estrogen receptors have been identified. These vary in proportion from tissue to tissue.

Circulating estrogens modulate the pituitary secretion of the gonadotropins, luteinizing hormone (LH), and FSH, through a negative feedback mechanism. Estrogens act to reduce the elevated levels of these hormones seen in postmenopausal women.

Endogenous progesterone is secreted by the ovary, placenta, and adrenal gland. In the presence of adequate estrogen, progesterone transforms a proliferative endometrium into a secretory endometrium.

Progesterone enhances cellular differentiation and generally opposes the actions of estrogens by decreasing estrogen receptor levels, increasing local metabolism of estrogens to less active metabolites, or inducing gene products that blunt cellular responses to estrogen. Progesterone exerts its effects in target cells by binding to specific progesterone receptors that interact with progesterone response elements in target genes. Progesterone receptors have been identified in the female reproductive tract, breast, pituitary, hypothalamus, and central nervous system.

12.2 Pharmacodynamics

Generally, a serum estrogen concentration does not predict an individual woman's therapeutic response to BIJUVA nor her risk for adverse outcomes. Likewise, exposure comparisons across different estrogen products to infer efficacy or safety for the individual woman may not be valid.

12.3 Pharmacokinetics

Absorption

The oral absorption of both estradiol and progesterone is subject to first-pass metabolism. After multiple doses of BIJUVA (estradiol and progesterone) capsules administered with food, the tmax (the time at which the maximum concentration is attained) for estradiol is approximately 3 to 6 hours and approximately 3 hours for progesterone (Figure 1, Figure 2, and Table 2, below).

Steady state for both estradiol and progesterone components of BIJUVA, as well as estradiol's main metabolite, estrone, is achieved within seven days. A dose-dependent increase in AUC0-t and Cmax of estradiol and a slightly more than proportionality increase in AUC0-t and Cmax of estrone were observed when the dose of estradiol was increased from 0.5 mg/day to 1 mg/day (Table 2).

Figure 1: Mean Steady-State Serum Estradiol Concentrations Following Daily Oral Administration of 0.5 mg Estradiol/100 mg Progesterone or 1 mg Estradiol/100 mg Progesterone with Food (Baseline Adjusted, at Day 7)

Estradiol

time after dosing (hrs)

Figure 2: Mean Steady-State Serum Progesterone Concentrations Following Daily Oral Administration of 0.5 mg Estradiol/100 mg Progesterone or 1 mg Estradiol/100 mg Progesterone with Food (Baseline Adjusted, at Day 7)

Progesterone

time after dosing (hrs)

Table 2: Mean (SD) Steady-State Pharmacokinetic Parameters after Administration of Capsules Containing 0.5 mg Estradiol/100 mg Progesterone or 1 mg Estradiol/100 mg Progesterone with Food in Healthy Postmenopausal Women (Baseline Adjusted, at Day 7)
Dosage Strength (estradiol/progesterone) | BIJUVA 0.5 mg/100 mg Mean (SD) |  | BIJUVA 1 mg/100 mg Mean (SD)
Estradiol | N |  | N
AUC0-τ (pg∙h/mL) | 17 | 386.8 (356.6) | 20 | 772.4 (384.1)
Cmax (pg/mL) | 17 | 23.95 (16.86) | 20 | 42.27 (18.60)
Cavg (pg/mL) | 17 | 16.64 (14.50) | 19 | 33.99 (14.53)
tmax (h) [Median and range] | 17 | 6.00 (0.00 – 12.00) | 19 | 3.00 (0.67 – 18.03)
t½ (h) [Effective t½. Calculated as 24∙ln(2)/ ln (accumulation ratio/(accumulation ratio-1)) for subjects with accumulation ratio >1.] | 11 | 28.01 (9.99) | 19 | 26.47 (14.61)
Estrone
AUC0-τ (pg∙h/mL) | 17 | 1981 (976.0) | 20 | 4594 (2138)
Cmax (pg/mL) | 17 | 108.0 (48.58) | 20 | 238.5 (100.4)
Cavg (pg/mL) | 17 | 82.81 (40.80) | 20 | 192.1 (89.43)
tmax (h) | 17 | 11.98 (2.00 – 18.00) | 20 | 5.00 (1.50 – 12.00)
t½ (h) | 17 | 20.46 (5.61) | 19 | 22.37 (7.64)
Progesterone
AUC0-τ (ng∙h/mL) | 17 | 12.19 (11.01) | 20 | 18.05 (15.58)
Cmax (ng/mL) | 17 | 4.40 (5.72) | 20 | 11.31 (23.10)
Cavg (ng/mL) | 17 | 0.55 (0.45) | 20 | 0.76 (0.65)
tmax (h) | 17 | 2.00 (0.67 – 8.00) | 20 | 2.51 (0.67 – 6.00)
t½ (h) | 13 | 8.77 (2.78) | 18 | 9.98 (2.57)
Abbreviations: AUC0-τ = area under the concentration vs time curve within the dosing interval at steady-state, Cavg = average concentration at steady-state, Cmax = maximum concentration, SD = standard deviation, tmax = time to maximum concentration, t½ = half-life

Food Effect

Concomitant food ingestion increased the AUC and Cmax of the progesterone component of BIJUVA relative to a fasting state when administered at a dose of 100 mg. In a study where BIJUVA was administered to postmenopausal women at a dose of 1 mg estradiol/100 mg progesterone within 30 minutes of starting a high-fat meal, the Cmax and AUC of progesterone were 162% and 79% higher, respectively, relative to the fasting state and the median tmax of progesterone was delayed from 2 hours to 3 hours. Concomitant food ingestion had no effect on the AUC of the estradiol component of BIJUVA but decreased Cmax by approximately 54% and delayed median tmax from 1 hour to 12 hours.

Distribution

Estradiol

The distribution of exogenous estrogens is similar to that of endogenous estrogens. Estrogens are widely distributed in the body and are generally found in higher concentrations in the sex hormone target organs. Estrogens circulating in the blood largely are bound to SHBG and albumin.

Progesterone

Progesterone is approximately 96% to 99% bound to serum proteins, primarily to serum albumin (50% to 54%) and transcortin (43% to 48%).

Elimination

Following repeat dosing with BIJUVA (estradiol and progesterone) capsules, 0.5 mg/100 mg or 1 mg/100 mg, the half-life of estradiol was 28 ± 10 hours and 26 ± 15 hours, respectively, and the half-life of progesterone was 9 ± 3 hours and 10 ± 3 hours, respectively (Table 2).

Metabolism

Estradiol

Exogenous estrogens are metabolized in the same manner as endogenous estrogens. Circulating estrogens exist in a dynamic equilibrium of metabolic interconversions. These transformations take place mainly in the liver. Estradiol is converted reversibly to estrone, and both can be converted to estriol, the major urinary metabolite. Estrogens also undergo enterohepatic recirculation via sulfate and glucuronide conjugation in the liver, biliary secretion of conjugates into the intestine, and hydrolysis in the intestine followed by reabsorption. In postmenopausal women, a significant portion of the circulating estrogens exist as sulfate conjugates, especially estrone sulfate, which serves as a circulating reservoir for the formation of more active estrogens.

Progesterone

Progesterone is metabolized primarily by the liver largely to pregnanediols and pregnanolones. Pregnanediols and pregnanolones are conjugated in the liver to glucuronide and sulfate metabolites. Progesterone metabolites, which are excreted in the bile, may be deconjugated and may be further metabolized in the intestine via reduction, dehydroxylation, and epimerization.

Excretion

Estradiol

Estradiol, estrone, and estriol are excreted in the urine along with glucuronide and sulfate conjugates.

Progesterone

The glucuronide and sulfate conjugates of pregnanediol and pregnanolone are excreted in the bile and urine. Progesterone metabolites are eliminated mainly by the kidneys. Progesterone metabolites which are excreted in the bile may undergo enterohepatic recycling or may be excreted in the feces.

13 NONCLINICAL TOXICOLOGY

13.1 Carcinogenesis, Mutagenesis, Impairment of Fertility

Long-term continuous administration of natural and synthetic estrogens in certain animal species increases the frequency of carcinomas of the breast, uterus, cervix, vagina, testis, and liver.

Progesterone has not been tested for carcinogenicity in animals by the oral route of administration. When implanted into female mice, progesterone produced mammary carcinomas, ovarian granulosa cell tumors, and endometrial stromal sarcomas. In dogs, long-term intramuscular injections produced nodular hyperplasia and benign and malignant mammary tumors. Subcutaneous or intramuscular injections of progesterone decreased the latency period and increased the incidence of mammary tumors in rats previously treated with a chemical carcinogen.

Progesterone did not show evidence of genotoxicity in in vitro studies for point mutations or for chromosomal damage. In vivo studies for chromosome damage have yielded positive results in mice at oral doses of 1000 mg/kg and 2000 mg/kg. Exogenously administered progesterone has been shown to inhibit ovulation in a number of species and it is expected that high doses given for an extended duration would impair fertility until the cessation of treatment.

14 CLINICAL STUDIES

14.1 Effects on Vasomotor Symptoms in Postmenopausal Women

The effectiveness and safety of BIJUVA (estradiol and progesterone) capsules, 0.5 mg/100 mg and 1 mg/100 mg, on moderate to severe vasomotor symptoms (hot flushes) due to menopause were examined in a 12-week randomized, double-blind, placebo-controlled substudy of a single 52-week safety study. A total of 726 postmenopausal women were randomized to multiple dose combinations of estradiol and progesterone, and placebo; these women were 40 to 65 years of age (mean 54.6 years) and had at least 50 moderate to severe vasomotor symptoms per week at baseline. The mean number of years since last menstrual period was 5.9 years, with all women undergoing natural menopause. The primary efficacy population consisted of women who self- identified their race as: White (67%), Black/African American (31%), and "Other" (2.1%). In the substudy evaluating effects on moderate to severe vasomotor symptoms, a total of 149 women received BIJUVA (estradiol and progesterone) capsules, 0.5 mg/100 mg, 141 women received BIJUVA (estradiol and progesterone) capsules, 1 mg/100 mg, and 135 women received placebo.

The evaluated co-primary efficacy endpoints included: 1) mean weekly reduction in frequency of moderate to severe vasomotor symptoms with BIJUVA compared to placebo at Weeks 4 and 12 and 2) mean weekly reduction in severity of moderate to severe vasomotor symptoms with BIJUVA compared to placebo at Weeks 4 and 12.

Overall, BIJUVA (estradiol and progesterone) capsules, 0.5 mg/100 mg and 1 mg/100 mg, statistically significantly reduced both the frequency and severity of moderate to severe vasomotor symptoms from baseline compared with placebo at Weeks 4 and 12. The change from baseline in the frequency and severity of vasomotor symptoms observed and the difference from placebo are shown in Table 3 and Table 4, respectively.

Table 3: Mean Weekly Change from Baseline and Difference from Placebo in the Frequency of Moderate to Severe Vasomotor Symptoms
 | BIJUVA 0.5 mg/100 mg (N=149) | BIJUVA 1 mg/100 mg (N=141) | Placebo (N=135)
Week 4 | n=144 | n=134 | n=126
Baseline | 72.3 (28.06) | 72.1 (27.80) | 72.3 (23.44)
Mean (SD) change from baseline | -35.1 (29.14) | -40.6 (30.59) | -26.4 (27.05)
Difference from placebo [Least square mean difference (SE) from placebo] | -8.07 (3.25) | -12.81 (3.30) | ---
P-value [P-value of least square mean difference from placebo using mixed model repeated measures analyses] | 0.013 | < 0.001 | ---
Week 12 | n=129 | n=124 | n=115
Baseline | 72.8 (28.96) | 72.2 (25.04) | 72.2 (22.66)
Mean (SD) change from baseline | -53.7 (31.93) | -55.1 (31.36) | -40.2 (29.79)
Difference from placebo | -15.07 (3.39) | -16.58 (3.44) | ---
P-value | <0.001 | <0.001 | ---
Definitions: SD – standard deviation; SE – standard error

Table 4: Mean Weekly Change from Baseline and Difference from Placebo in the Severity of Moderate to Severe Vasomotor Symptoms
 | BIJUVA 0.5 mg/100 mg (N=149) | BIJUVA 1 mg/100 mg (N=141) | Placebo (N=135)
Week 4 | n=144 | n=134 | n=126
Baseline | 2.51 (0.248) | 2.54 (0.325) | 2.52 (0.249)
Mean (SD) change from baseline | -0.51 (0.563) | -0.48 (0.547) | -0.34 (0.386)
Difference from placebo [Least square mean difference (SE) from placebo] | -0.17 (0.060) | -0.13 (0.061) | ---
P-value [P-value of least square mean difference from placebo using mixed model repeated measures analyses] | 0.005 | 0.031 | ---
Week 12 | n=129 | n=124 | n=115
Baseline | 2.51 (0.248) | 2.55 (0.235) | 2.52 (0.245)
Mean (SD) change from baseline | -0.90 (0.783) | -1.12 (0.963) | -0.56 (0.603)
Difference from placebo | -0.39 (0.099) | -0.57 (0.100) | ---
P-value | <0.001 | <0.001 | ---
Definitions: SD – standard deviation; SE – standard error

Adjusting for potential confounders such as BMI, smoking, alcohol use, and baseline estradiol level, treatment with BIJUVA (estradiol and progesterone) capsules, 0.5 mg/100 mg or 1 mg/100 mg, did not demonstrate statistically significant reductions in both frequency and severity of moderate to severe vasomotor symptoms by Week 12 in women who self-identified as Black/African Americans (data not shown).

14.2 Effects on Endometrium in Postmenopausal Women

Effects of BIJUVA (estradiol and progesterone) capsules, 0.5 mg/100 mg and 1 mg/100 mg, on endometrial hyperplasia and endometrial malignancy were assessed in the 52-week safety trial. The Endometrial Safety population included women who had taken at least one dose of BIJUVA (estradiol and progesterone) capsules, 0.5 mg/100 mg or 1 mg/100 mg, and had baseline and post-baseline endometrial biopsies. During the trial, endometrial biopsy assessments revealed one (1) case of endometrial hyperplasia and no cases of endometrial cancer in women who received BIJUVA (estradiol and progesterone) 0.5 mg/100 mg capsules, one (1) case of endometrial hyperplasia and no cases of endometrial cancer in women who received BIJUVA (estradiol and progesterone) 1 mg/100 mg capsules, and no cases of endometrial hyperplasia or endometrial cancer in women who received placebo (see Table 5).

Table 5: Incidence of Endometrial Hyperplasia After up to 12 Months of Treatment
 | BIJUVA 0.5 mg/100 mg (N=303) | BIJUVA 1 mg/100 mg (N=281) | Placebo (N=92)
Hyperplasia incidence rate % (n/N) | 1/303 (0.33) | 1/281 (0.36) | 0/92 (0.00)
One-sided upper 95% confidence limit | 1.83 | 1.97 | 3.93

Six (6) cases of disordered proliferative endometrium were reported for BIJUVA (estradiol and progesterone) capsules, 0.5 mg/100 mg, and four (4) cases of disordered proliferative endometrium were also reported for BIJUVA (estradiol and progesterone) capsules, 1 mg/100 mg, in the 52-week safety trial.

14.3 Effects on Uterine Bleeding or Spotting in Postmenopausal Women

Uterine bleeding or spotting was evaluated in the 52-week safety study by daily diary. At 52 weeks, cumulative amenorrhea was reported by 67.6% of women who received BIJUVA (estradiol and progesterone) capsules, 0.5 mg/100 mg, 56.1% of women who received BIJUVA (estradiol and progesterone) capsules, 1 mg/100 mg, and 78.9% who received placebo.

14.4 Women's Health Initiative Estrogen Plus Progestin Trial

The WHI estrogen plus progestin trial enrolled predominantly healthy postmenopausal women to assess the risks and benefits of daily oral CE (0.625 mg) in combination with MPA (2.5 mg) compared to placebo in the prevention of certain chronic diseases. The primary endpoint was the incidence of CHD (defined as nonfatal MI, silent MI and CHD death), with invasive breast cancer as the primary adverse outcome. A "global index" included the earliest occurrence of CHD, invasive breast cancer, stroke, PE, endometrial cancer, colorectal cancer, hip fracture, or death due to other causes. This trial did not evaluate the effects of CE plus MPA on menopausal symptoms.

The WHI estrogen plus progestin trial was stopped early. After an average follow-up of 5.6 years of treatment, the increased risk of invasive breast cancer crossed the predefined stopping threshold. The global index was supportive of a finding of overall harm. The absolute excess risk of events included in the global index was 19 per 10,000 women-years.

Results of the trial, which enrolled 16,608 women (average 63 years of age, range 50 to 79; 83.9% White, 6.8% Black, 5.4% Hispanic, 3.9% Other) are presented in Table 6. These results reflect centrally adjudicated data after an average follow-up of 5.6 years.^6,7

Table 6: Relative Risk and Risk Difference Observed in the WHI Estrogen Plus Progestin Trial at an Average of 5.6 Years [Adapted from 2013 WHI substudy (CE/MPA n=8,506, placebo n=8,102). WHI publications can be viewed at www.nhlbi.nih.gov/whi.] , [Results are based on centrally adjudicated data]
Event | Relative Ratio (95% CI) [In the WHI studies, hazard ratios were estimated using Cox proportional hazards models comparing treatment to placebo; however, they are described here as relative risks. Nominal confidence intervals unadjusted for multiple looks and multiple comparisons.] | Risk Difference (CEMPA vs placebo/10,000 WYs)
CHD events | 1.18 (0.95-1.45) | 6 (41 vs 35)
Non-fatal MI | 1.24 (0.98-1.56) | 6 (35 vs 29)
CHD death | 1.05 (0.76-1.45) | 1 (16 vs 15)
All Strokes | 1.37 (1.07-1.76) | 9 (33 vs 24)
Deep vein thrombosis [Not included in "global index."] | 1.87 (1.37-2.54) | 12 (25 vs 14)
Pulmonary embolism | 1.98 (1.36-2.87) | 9 (18 vs 9)
Invasive breast cancer [Includes metastatic and non-metastatic breast cancer with the exception of in situ cancer.] | 1.24 (1.01-1.53) | 9 (43 vs 35)
Colorectal cancer | 0.62 (0.43-0.89) | -6 (10 vs 17)
Endometrial cancer | 0.83 (0.49-1.40) | -1 (6 vs 7)
Hip fracture | 0.67 (0.47-0.95) | -6 (11 vs 17)
Vertebral fracture | 0.68 (0.48-0.96) | -6 (12 vs 17)
Total factures | 0.76 (0.69-0.83) | -51 (161 vs 212)
Overall mortality, [All deaths, except from breast or colorectal cancer, definite or probable CHD, PE or cerebrovascular disease.] | 0.97 (0.81-1.16) | -1 (52 vs 53)
Global Index [A subset of the events was combined in a "global index," defined as the earliest occurrence of CHD events, invasive breast cancer, stroke, PE, colorectal cancer, hip fracture, or death due to other causes.] | 1.12 (1.02-1.24) | 20 (189 vs 168)

Timing of the initiation of estrogen plus progestin therapy relative to the start of menopause may affect the overall risk benefit profile. The results of the WHI estrogen plus progestin trial in women 50-59 years of age (N=2,837 for CE/MPA; N=2,683 for placebo) are shown in Table 7.

Table 7: Relative Risk and Risk Difference Observed Among Women 50-59 Years of Age in the WHI Estrogen Plus Progestin Trial at an Average of 5.8 Years [Adapted from 2013 WHI trial (CE/MPA n=2,837; placebo=2,683). WHI publications can be viewed at www.nhlbi.nih.gov/whi.] , [Results are based on centrally adjudicated data.]
Event | Relative Ratio (95% CI) [In the WHI studies, hazard ratios were estimated using Cox proportional hazards models comparing treatment to placebo; however, they are described here as relative risks. Nominal confidence intervals unadjusted for multiple looks and multiple comparisons.] | Risk Difference (CEMPA vs placebo/10,000 WYs)
CHD events | 1.34 (0.82-2.19) | 5 (23 vs 17)
Non-fatal MI | 1.32 (0.77-2.25) | 4 (19 vs 15)
CHD death | 0.77 (0.33-1.79) | -2 (6 vs 8)
All Strokes | 1.51 (0.81-2.82) | 5 (15 vs 10)
Deep vein thrombosis [Not included in "global index."] | 3.01 (1.36-6.66) | 10 (15 vs 5)
Pulmonary embolism | 2.05 (0.89-4.71) | 6 (11 vs 5)
Invasive breast cancer [Includes metastatic and non-metastatic breast cancer with the exception of in situ cancer.] | 1.21 (0.81-1.80) | 6 (33 vs 27)
Colorectal cancer | 0.79 (0.29-2.18) | -1 (4 vs 5)
Endometrial cancer | 1.07 (0.33-3.53) | 0 (4 vs 3)
Hip fracture | 0.17 (0.22-1.45) | -3 (1 vs 3)
Vertebral fracture | 0.38 (0.15-0.97) | -6 (4 vs 10)
Total factures | 0.82 (0.68-1.00) | -25 (120 vs 145)
Overall mortality, [All deaths, except from breast or colorectal cancer, definite or probable CHD, PE or cerebrovascular disease.] | 0.67 (0.43-1.04) | -10 (21 vs 31)
Global Index [A subset of the events was combined in a "global index," defined as the earliest occurrence of CHD events, invasive breast cancer, stroke, PE, colorectal cancer, hip fracture, or death due to other causes.] | 1.12 (0.89-1.40) | 12 (103 vs 91)

14.5 Women's Health Initiative Memory Study

The WHIMS estrogen plus progestin ancillary study of WHI enrolled 4,532 predominantly healthy postmenopausal women 65 years of age and older (47% were 65 to 69 years of age 35% were 70 to 74 years; 18% were 75 years of age and older) to evaluate effects of daily CE (0.625 mg) plus MPA (2.5 mg) on the incidence of probable dementia (primary outcome) compared to placebo. Probable dementia as defined in this study included Alzheimer's disease (AD), vascular dementia (VaD), and mixed types (having features of both AD and VaD). The most common classification of probable dementia in the treatment group and the placebo group was AD.

After an average follow-up of 4 years, the relative risk of probable dementia for CE/MPA versus placebo was 2.01 (95% CI, 1.19 to -3.42), with a risk difference of 23 per 10,000 WYs (46 versus 23). Since the ancillary study was conducted in women 65 to 79 years of age, it is unknown whether these findings apply to younger postmenopausal women [see Use in Specific Populations (8.5)].^8

15 REFERENCES

1. Manson, J. E., et al Menopausal hormone therapy and health outcomes during the intervention and extended poststopping phases of the Women's Health Initiative randomized trials. JAMA, 310(13): 1353–1368 (2013). https://doi.org/10.1001/jama.2013.278040
2. Hulley S, Grady D, Bush T, Furberg C, Herrington D, Riggs B, Vittinghoff E. Randomized trial of estrogen plus progestin for secondary prevention of coronary heart disease in postmenopausal women. Heart and Estrogen/progestin Replacement Study (HERS) Research Group. JAMA. 1998 Aug 19;280(7):605-13. doi: 10.1001/jama.280.7.605. PMID: 9718051.
3. Grady D, Herrington D, Bittner V, Blumenthal R, Davidson M, Hlatky M, Hsia J, Hulley S, Herd A, Khan S, Newby LK, Waters D, Vittinghoff E, Wenger N; HERS Research Group. Cardiovascular disease outcomes during 6.8 years of hormone therapy: Heart and Estrogen/progestin Replacement Study followup (HERS II). JAMA. 2002 Jul 3;288(1):49-57. doi: 10.1001/jama.288.1.49. Erratum in: JAMA 2002 Sep 4;288(9):1064. PMID 12090862.
4. Collaborative Group on Hormonal Factors in Breast Cancer. Type and timing of menopausal hormone therapy and breast cancer risk: individual participant meta-analysis of the worldwide epidemiological evidence. Lancet. 2019 Sep 28;394(10204):1159-1168. doi: 10.1016/S0140-6736(19)31709-X. Epub 2019 Aug 29. PMID: 31474332; PMCID: PMC6891893.
5. Collaborative Group On Epidemiological Studies Of Ovarian Cancer; Beral V, Gaitskell K, Hermon C, Moser K, Reeves G, Peto R. Menopausal hormone use and ovarian cancer risk: individual participant meta-analysis of 52 epidemiological studies. Lancet. 2015 May 9;385(9980):1835-42. doi:10.1016/S0140-6736(14)61687-1. Epub 2015 Feb 13. PMID: 25684585; PMCID: PMC4427760.

16 HOW SUPPLIED/STORAGE AND HANDLING

16.1 How Supplied

BIJUVA (estradiol and progesterone) capsules, 0.5 mg/100 mg, are oval-shaped opaque capsules, which are light pink on one side and dark pink on the other side. Each capsule is imprinted in white ink indicating the dosage strength (5C1). BIJUVA (estradiol and progesterone) capsules, 0.5 mg/100 mg, are provided in a blister package of 30 capsules.

BIJUVA (estradiol and progesterone) capsules, 1 mg/100 mg, are oval-shaped opaque capsules, which are light pink on one side and dark pink on the other side. Each capsule is imprinted in white ink indicating the dosage strength (1C1). BIJUVA (estradiol and progesterone) capsules, 1 mg/100 mg, are provided in a blister package of 30 capsules.

BIJUVA (estradiol and progesterone) capsules, 0.5 mg/100 mg | NDC 50261-251-30
BIJUVA (estradiol and progesterone) capsules, 1 mg/100 mg | NDC 50261-211-30

Keep out of reach of children. Packages are not child-resistant.

16.2 Storage and Handling

Store at 20°C to 25°C (68°F to 77°F), excursions permitted to 15°C to 30°C (59°F to 86°F). [See USP Controlled Room Temperature]

17 PATIENT COUNSELING INFORMATION

Advise women to read the FDA-approved patient labeling (Patient Information).

Vaginal Bleeding

Inform postmenopausal women to report any vaginal bleeding to their healthcare provider as soon as possible [see Warnings and Precautions (5.2)].

Possible Serious Adverse Reactions with Estrogen Plus Progestogen Therapy

Inform postmenopausal women of possible serious adverse reactions of estrogen plus progestogen therapy including cardiovascular disorders and malignant neoplasms [see Warnings and Precautions (5.1, 5.2)].

Possible Common Adverse Reactions with Estrogen Plus Progestogen Therapy

Inform postmenopausal women of possible less serious but common adverse reactions of estrogen plus progestogen therapy such as breast tenderness, headache, nausea, vaginal bleeding, vaginal discharge, and pelvic pain [see Adverse Reactions (6.1)].

Missed Evening Dose of BIJUVA

Advise the woman that if she misses her evening dose, she should take the dose with food as soon as she can, unless it is within two hours of the next evening dose.

PATIENT INFORMATION
BIJUVA® (bī jooꞌ vah)
(estradiol and progesterone)
capsules, for oral use

What is the most important information I should know about BIJUVA (a combination of estrogen and progestogen)?

- Do not use estrogens with or without progestogens to prevent heart disease, heart attacks, strokes, or dementia (decline of brain function).
- Using estrogens with progestogens may increase your chances of getting heart attacks, strokes, breast cancer, or blood clots.

What is BIJUVA?

- BIJUVA is a prescription medicine that contains two kinds of hormones, an estrogen and a progestogen.

What is BIJUVA used for?
BIJUVA is used after menopause to reduce moderate to severe hot flashes.
Estrogens are hormones made by a woman's ovaries. The ovaries normally stop making estrogens when a woman is between 45 and 55 years old. This drop in body estrogen levels causes the "change of life" or menopause (the end of monthly menstrual periods). Sometimes, both ovaries are removed during an operation before natural menopause takes place. The sudden drop in estrogen levels causes "surgical menopause."
When estrogen levels begin dropping, some women get very uncomfortable symptoms, such as feelings of warmth in the face, neck, and chest, or sudden intense feelings of heat and sweating ("hot flashes" or "hot flushes"). In some women the symptoms are mild, and they will not need to take estrogens. In other women, symptoms can be more severe.

Who should not use BIJUVA?
Do not use BIJUVA if you have had your uterus (womb) removed (hysterectomy).
BIJUVA contains a progestogen to decrease the chance of getting cancer of the uterus. If you do not have a uterus, you do not need a progestogen and you should not use BIJUVA.

Do not start using BIJUVA if you:

- have any unusual vaginal bleeding.
  Vaginal bleeding after menopause may be a warning sign of cancer of the uterus (womb). Your healthcare provider should check any unusual vaginal bleeding to find out the cause.
- have been diagnosed with a bleeding disorder.
- currently have or have had certain cancers.
  Estrogens may increase the chances of getting certain types of cancers, including cancer of the breast or uterus (womb). If you have or have had cancer, talk with your healthcare provider about whether you should use BIJUVA.
- currently have or have had blood clots.
- had a stroke or heart attack.
- currently have or have had liver problems.
- are allergic to BIJUVA or any of its ingredients. See the list of ingredients in BIJUVA at the end of this leaflet.

Before you use BIJUVA, tell your healthcare provider about all of your medical conditions, including if you:

- have high levels of fat in your blood (triglycerides).
- have any unusual vaginal bleeding. Vaginal bleeding after menopause may be a warning sign of cancer of the uterus (womb). Your healthcare provider should check any unusual vaginal bleeding to find out the cause.
- have any other medical conditions that may become worse while you are using BIJUVA. Your healthcare provider may need to check you more carefully if you have certain conditions, such as:

- asthma (wheezing)
- diabetes
- a genetic problem called porphyria
- lupus
- hypertension (high blood pressure)
- have high calcium in your blood

- epilepsy (seizures)
- migraine
- endometriosis
- angioedema (swelling of face or tongue)
- problems with your heart, liver, thyroid or kidneys

- are going to have surgery or will be on bed rest. Your healthcare provider will let you know if you need to stop using BIJUVA.
- are pregnant or think you may be pregnant. BIJUVA is not for pregnant women.
- are breastfeeding. The hormones in BIJUVA can pass into your breast milk.

Tell your healthcare provider about all the medicines you take, including prescription and over-the-counter medicines, vitamins, and herbal supplements. Some medicines may affect how BIJUVA works. Some other medicines and food products may increase or decrease the concentrations of the hormones in BIJUVA in the blood. BIJUVA may affect how your other medicines work, and other medicines may affect how BIJUVA works. Keep a list of your medicines and show it to your healthcare provider and pharmacist when you get new medicine.

How should I use BIJUVA?

- Take BIJUVA exactly as your healthcare provider tells you to take it.
- Take 1 capsule by mouth each evening with food.
- If you miss a dose of BIJUVA, take the missed dose as soon as possible with food, unless it is within two hours of the next evening dose of BIJUVA.
- Estrogens should be used at the lowest dose possible for your treatment and only as long as needed. You and your healthcare provider should talk regularly (for example, every 3 to 6 months) about whether you still need treatment with BIJUVA.

What are the possible side effects of BIJUVA?
Side effects are grouped by how serious they are and how often they happen when you are treated.
Serious but less common side effects include:

- heart attack
- stroke
- blood clots
- breast cancer
- cancer of the lining of the uterus (womb)
- cancer of the ovary
- dementia
- gallbladder disease
- high or low blood calcium levels
- changes in vision

- high blood pressure
- high levels of fat in your blood (triglycerides)
- liver problems
- changes in thyroid hormone levels
- swelling or fluid retention
- cancer changes of endometriosis
- enlargement of benign tumors of the uterus ("fibroids")
- worsening swelling of face or tongue (angioedema) in women who have a history of angioedema
- changes in laboratory test results such as bleeding time and high blood sugar levels

Call your healthcare provider right away if you get any of the following warning signs or any other unusual symptoms that concern you:

- new breast lumps
- unusual vaginal bleeding
- changes in vision or speech
- sudden new severe headaches
- severe pains in your chest or legs with or without shortness of breath, weakness and fatigue
- vomiting

Common side effects of BIJUVA include:

- breast tenderness
- headache

- nausea
- vaginal bleeding

- vaginal discharge
- pelvic pain

Tell your healthcare provider if you have any side effects that bother you or do not go away.
These are not all of the possible side effects of BIJUVA. Call your doctor for medical advice about side effects. You may report side effects to FDA at 1-800-FDA-1088. You may also report side effects to Mayne Pharma at 1-844-825-8500.

What can I do to lower my chances of a serious side effect with BIJUVA?

- Talk with your healthcare provider regularly about whether you should continue using BIJUVA.
- If you have a uterus, talk with your healthcare provider about whether BIJUVA is right for you.
- In general, the addition of a progestogen is recommended for a woman with a uterus to reduce the chance of getting cancer of the uterus (womb).
- See your healthcare provider right away if you get vaginal bleeding while using BIJUVA.
- Have a pelvic exam, breast exam and mammogram (breast X-ray) every year unless your healthcare provider tells you something else.
- If members of your family have had breast cancer or if you have ever had breast lumps or an abnormal mammogram (breast X-ray), you may need to have breast exams more often.
- If you have high blood pressure, high cholesterol (fat in the blood), diabetes, are overweight, or if you use tobacco, you may have higher chances for getting heart disease.

Ask your healthcare provider for ways to lower your chances for getting heart disease.

How should I store BIJUVA?

- Store at room temperature between 68°F to 77°F (20°C to 25°C).
- Keep BIJUVA and all medicines out of the reach of children.

General information about the safe and effective use of BIJUVA.
Medicines are sometimes prescribed for purposes other than those listed in a Patient Information leaflet. Do not use BIJUVA for a condition for which it was not prescribed. Do not give BIJUVA to other people, even if they have the same symptoms that you have. It may harm them. You can ask your pharmacist or healthcare provider for information about BIJUVA that is written for health professionals.

What are the ingredients in BIJUVA?
Active ingredients: estradiol and progesterone.
Inactive ingredients: ammonium hydroxide, ethanol, ethyl acetate, FD&C Red #40, gelatin, glycerin, hydrolyzed gelatin, isopropyl alcohol, lauroyl polyoxyl-32 glycerides, lecithin, medium chain mono and di-glycerides, medium chain triglycerides, polyethylene glycol, polyvinyl acetate phthalate, propylene glycol, purified water, and titanium dioxide.
BIJUVA is supplied in blister cartons of 30 capsules.
For information, go to www.TherapeuticsMD.com or call TherapeuticsMD, Inc. at 1-877-833-0176.
Manufactured for: TherapeuticsMD, Inc., Boca Raton, FL 33431
For patent information: www.TherapeuticsMD.com/patents
BIJUVA is a registered trademark of TherapeuticsMD, Inc.
©TherapeuticsMD, Inc. All rights reserved.

BJVA-LAB-20003.6
Revised 02/2026

This Patient Information has been approved by the U.S. Food and Drug Administration.

Principal Display Panel – 0.5 mg Carton Label

NDC 50261-251-30

Rx Only

Bijuva®

(estradiol and progesterone) capsules

0.5 mg/100 mg per capsule

TherapeuticsMD®

30 capsules

Principal Display Panel – 1 mg Carton Label

NDC 50261-211-30

Rx Only

Bijuva®

(estradiol and progesterone) capsules

1 mg/100 mg per capsule

TherapeuticsMD®

30 capsules